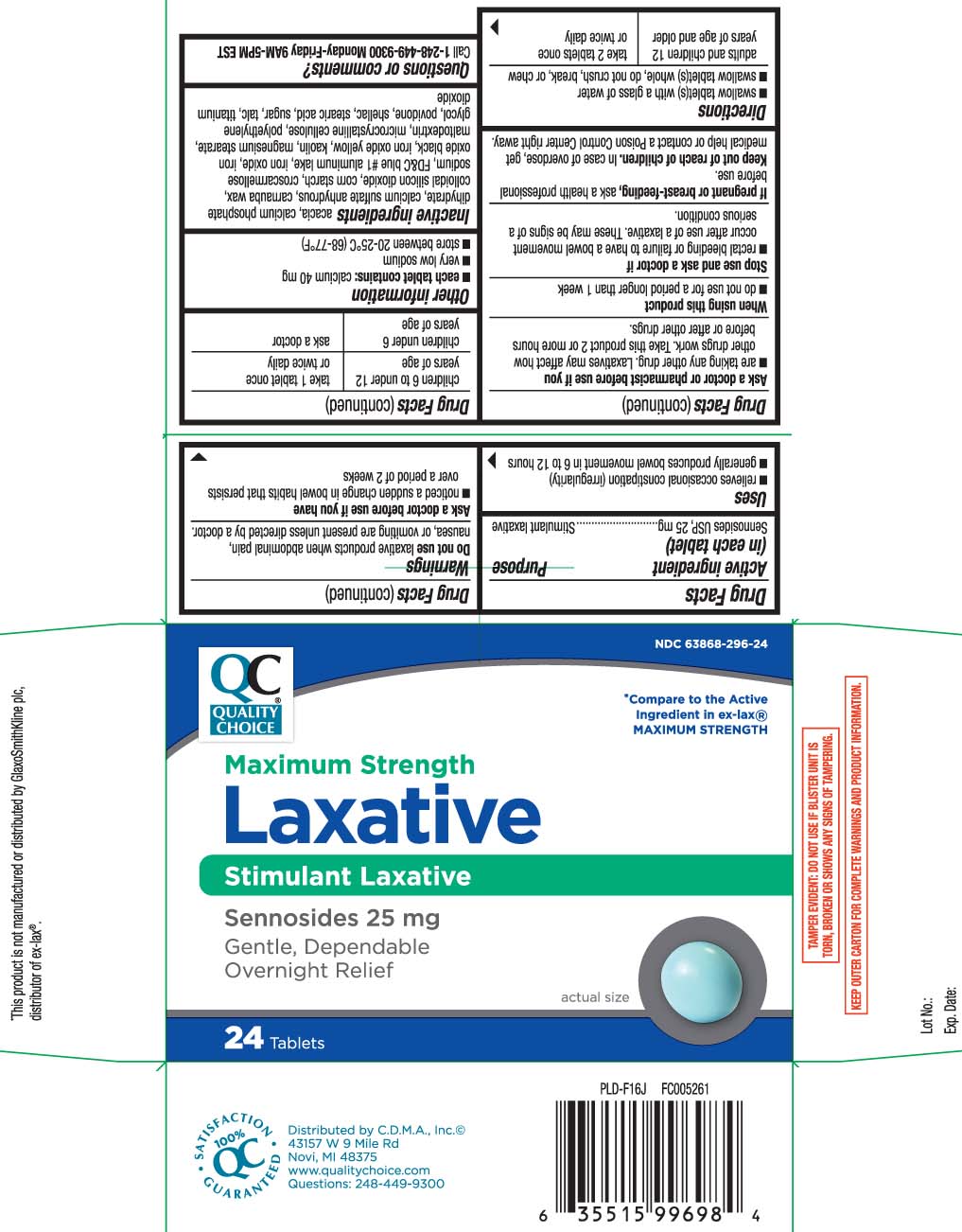 DRUG LABEL: Laxative Pills
NDC: 63868-296 | Form: TABLET
Manufacturer: QUALITY CHOICE (Chain Drug Marketing Association)
Category: otc | Type: HUMAN OTC DRUG LABEL
Date: 20231017

ACTIVE INGREDIENTS: SENNOSIDES 25 mg/1 1
INACTIVE INGREDIENTS: ACACIA; CALCIUM SULFATE ANHYDROUS; CARNAUBA WAX; SILICON DIOXIDE; STARCH, CORN; CROSCARMELLOSE SODIUM; CALCIUM PHOSPHATE, DIBASIC, DIHYDRATE; FD&C BLUE NO. 1; FERRIC OXIDE RED; FERROSOFERRIC OXIDE; FERRIC OXIDE YELLOW; KAOLIN; MAGNESIUM STEARATE; CELLULOSE, MICROCRYSTALLINE; POLYETHYLENE GLYCOL, UNSPECIFIED; POVIDONE; SHELLAC; STEARIC ACID; SUCROSE; TALC; TITANIUM DIOXIDE; MALTODEXTRIN

Drug Facts

Active ingredient (in each tablet)

Sennosides USP, 25 mg

Purpose

Stimulant laxative

Uses

- relieves occasional constipation (irregularity)
- generally produces bowel movement in 6 to 12 hours

Warnings

Do not use

laxative products when abdominal pain, nausea, or vomiting are present unless directed by a doctor.

Ask a doctor before use if you have

- noticed a sudden change in bowel habits that persists over a period of 2 weeks

Ask a doctor or pharmacist before use if you

- are taking any other drug. Laxatives may affect how other drugs work. Take this product 2 or more hours before or after other drugs.

When using this product

- do not use for a period longer than 1 week

Stop use and ask a doctor if

- rectal bleeding or failure to have a bowel movement occur after use of a laxative

These may be signs of a serious condition.

If pregnant or breast-feeding,

ask a health professional before use.

Keep out of reach of children.

In case of overdose, get medical help or contact a Poison Control Center right away.

Directions

- swallow tablet(s) with a glass of water
- swallow tablet(s) whole, do not crush, break, or chew

adults and children 12 years of age and older | take 2 tablets once or twice daily
children 6 to under 12 years of age | take 1 tablet once or twice daily
children under 6 years of age | ask a doctor

Other information

- each tablet contains: calcium 40 mg
- very low sodium
- store between 20-25ºC (68-77ºF)

Inactive ingredients

acacia, calcium phosphate dihydrate, calcium sulfate anhydrous, carnauba wax, colloidal silicon dioxide, corn starch, croscarmellose sodium, FD&C blue #1 aluminum lake, iron oxide*, iron oxide black, iron oxide yellow, kaolin, magnesium stearate, maltodextrin, microcrystalline cellulose, polyethylene glycol, povidone, shellac, stearic acid*, sugar,, talc, titanium dioxide

Questions or comments?

Call 1-248-449-9300 Monday-Friday 9AM-5PM EST

Principal Display Panel

*Compare to the active ingredient in ex-lax® MAXIMUM STRENGTH

Maximum Strength

Laxative

Stimulant Laxative

Sennosides USP, 25 mg

Gentle, Dependable Overnight Relief

Tablets

*This product is not manufactured or distributed by GlaxoSmithKline Ex-Lax®.plc, distributor of ex-lax®.

TAMPER EVIDENT: DO NOT USE IF BLISTER UNIT IS TORN, BROKEN OR SHOWS ANY SIGNS OF TAMPERING.

KEEP OUTER CARTON FOR COMPLETE WARNINGS AND PRODUCT INFORMATION.

Distributed by C.D.M.A., Inc.©

43157 W 9 Mile Rd

Novi, MI 48375

www.qualitychoice.com

Product Label

QUALITY CHOICE Maximum Strength Laxative